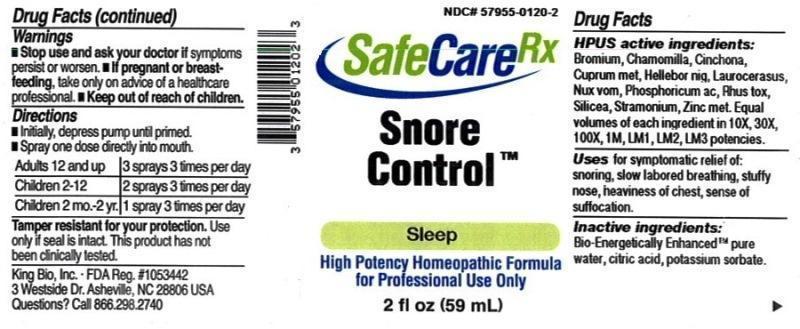 DRUG LABEL: Snore Control
NDC: 57955-0120 | Form: LIQUID
Manufacturer: King Bio Inc.
Category: homeopathic | Type: HUMAN OTC DRUG LABEL
Date: 20150319

ACTIVE INGREDIENTS: BROMINE 10 [hp_X]/59 mL; MATRICARIA RECUTITA 10 [hp_X]/59 mL; CINCHONA OFFICINALIS BARK 10 [hp_X]/59 mL; COPPER 10 [hp_X]/59 mL; HELLEBORUS NIGER ROOT 10 [hp_X]/59 mL; PRUNUS LAUROCERASUS LEAF 10 [hp_X]/59 mL; STRYCHNOS NUX-VOMICA SEED 10 [hp_X]/59 mL; PHOSPHORIC ACID 10 [hp_X]/59 mL; TOXICODENDRON PUBESCENS LEAF 10 [hp_X]/59 mL; SILICON DIOXIDE 10 [hp_X]/59 mL; DATURA STRAMONIUM 10 [hp_X]/59 mL; ZINC 10 [hp_X]/59 mL
INACTIVE INGREDIENTS: WATER; ANHYDROUS CITRIC ACID; POTASSIUM SORBATE

Snore Control™

ACTIVE INGREDIENT

Drug Facts__________________________________________________________________________________________________________

HPUS active ingredients: Bromium, Chamomilla, cinchona officinalis, Cuprum metallicum, Helleborus niger, Laurocerasus, Nux vomica, Phosphoricum acidum, Rhus toxicodendron, Silicea, Stramonium, Zincum metallicum. Equal volumes of each ingredient in 10X, 30X, 100X, 1M, LM1, LM2, LM3 potencies.

INDICATIONS AND USAGE

Uses for symptomatic relief of: snoring, slow labored breathing, stuffy nose, heaviness of chest, sense of suffocation.

Inactive Ingredients:

Bio-Energetically Enhanced™ pure water, citric acid and potassium sorbate.

Warnings

- Stop use and ask your doctor if symptoms persist or worsen.
- If pregnant or breast-feeding, take only on advice of a healthcare professional.

- Keep out of reach of children.

Directions

- Initially, depress pump until primed.
- Spray one dose directly into mouth.
- Adults 12 and up: 3 sprays 3 times per day.
- Children 2-12: 2 sprays 3 times per day.
- Children 2 mo-2yr: 1 spray 3 times per day.

OTHER SAFETY INFORMATION

Tamper resistant for your protection. Use only if safety seal is intact. This product has not been clinically tested.

PURPOSE

Uses for symptomatic relief of:

- snoring
- slow labored breathing
- stuffy nose
- heaviness of chest
- sense of suffocation